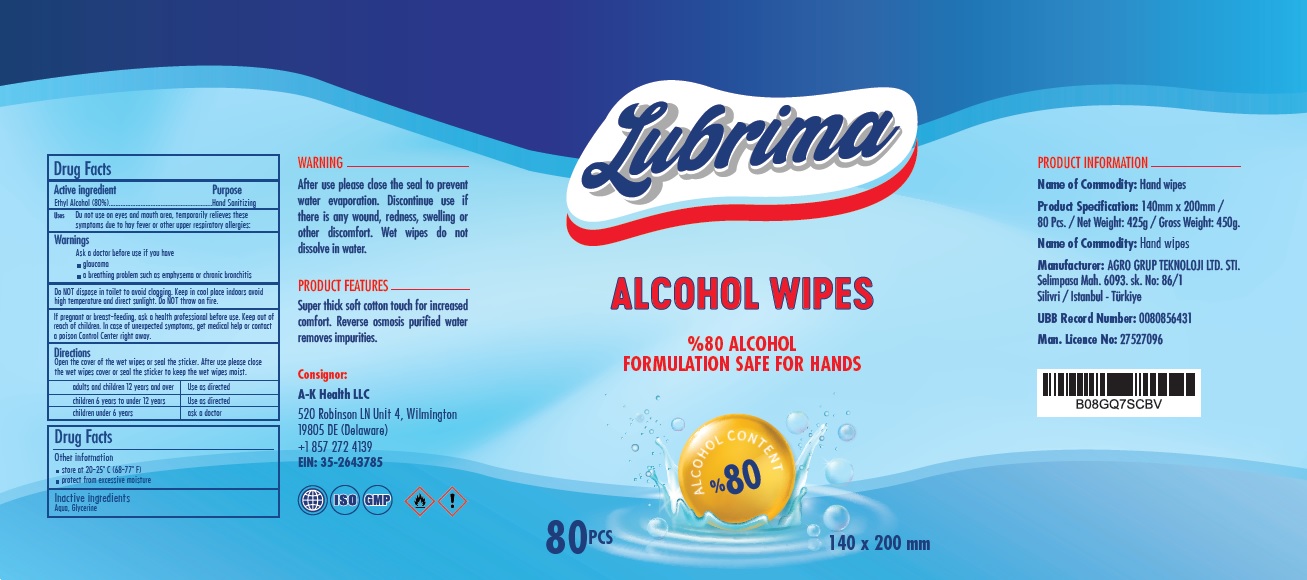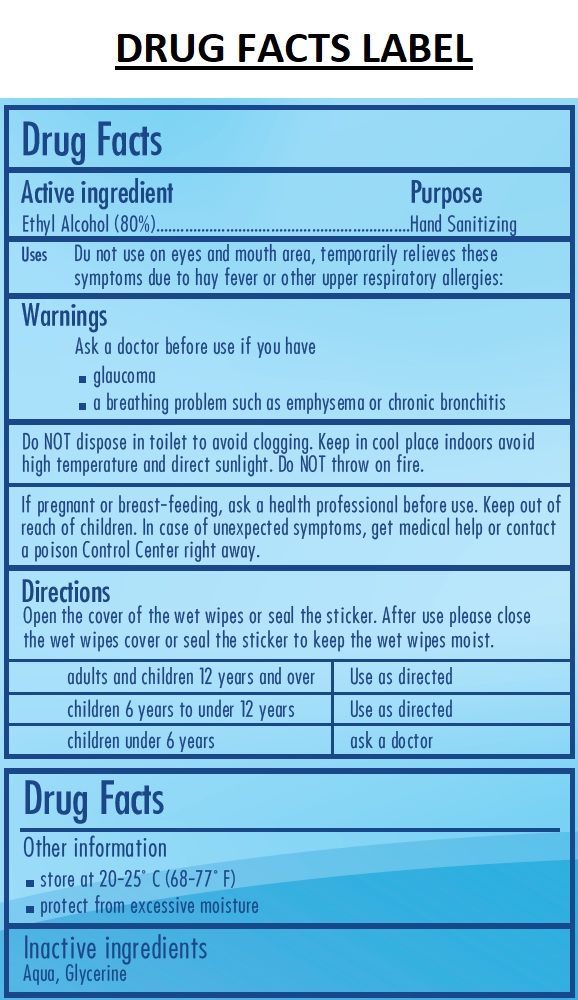 DRUG LABEL: LUBRIMA
NDC: 80481-101 | Form: CLOTH
Manufacturer: AGRO GRUP TEKNOLOJI BILGISAYAR SISTEMLERI TEMIZLIK MADDELERI SANAYI VE TICARET LIMITED SIR
Category: otc | Type: HUMAN OTC DRUG LABEL
Date: 20200904

ACTIVE INGREDIENTS: ALCOHOL 80 mL/100 mL
INACTIVE INGREDIENTS: WATER; GLYCERIN

Lubrima ALCOHOL WIPES

Active ingredient

Ethyl Alcohol (80%)

Purpose

Hand Sanitizing

INDICATIONS AND USAGE

Uses Do not use on eyes and mouth area, temporarily relieves these symptoms due to hay fever or other upper respiratory allergies:

Warnings

Ask a doctor before use if you have

• glaucoma

• a breathing problem such as emphysema or chronic bronchitis

Do NOT dispose in toilet to avoid clogging. Keep in cool place indoors avoid high temperature and direct sunlight. Do NOT throw on fire.

If pregnant or breast-feeding, ask a health professional before use.

Keep out of reach of children. In case of unexpected symptoms, get medical help or contact a poison Control Center right away.

Directions

Open the cover of the wet wipes or seal the sticker. After use please close the wet wipes cover or seal the sticker to keep the wet wipes moist.

adults and children 12 years and over | Use as directed
children 6 years to under 12 years | Use as directed
children under 6 years | ask a doctor

Other information

• store at 20-25° C (68-77° F)
• protect from excessive moisture

Inactive ingredients

Aqua, Glycerine

%80 ALCOHOL
FORMULATION SAFE FOR HANDS

ALCOHOL CONTENT %80

WARNING

After use please close the seal to prevent water evaporation. Discontinue use if there is any wound, redness, swelling or other discomfort. Wet wipes do not dissolve in water.

PRODUCT FEATURES

Super thick soft cotton touch for increased comfort. Reverse osmosis purified water removes impurities.

Consignor:
A-K Health LLC
520 Robinson LN Unit 4, Wilmington
19805 DE (Delaware)
+1 857 272 4139
EIN: 35-2643785

ISO

GMP

PRODUCT INFORMATION
Name of Commodity: Hand wipes
Product Specification: 140mm x 200mm / 80 Pcs. / Net Weight: 425g / Gross Weight: 450g.
Name of Commodity: Hand wipes
Manufacturer: AGRO GRUP TEKNOLOJI LTD. STI.

Selimpasa Mah. 6093. sk. No: 86/1
Silivri / Istanbul - Türkiye
UBB Record Number: 0080856431
Man. Licence No: 27527096